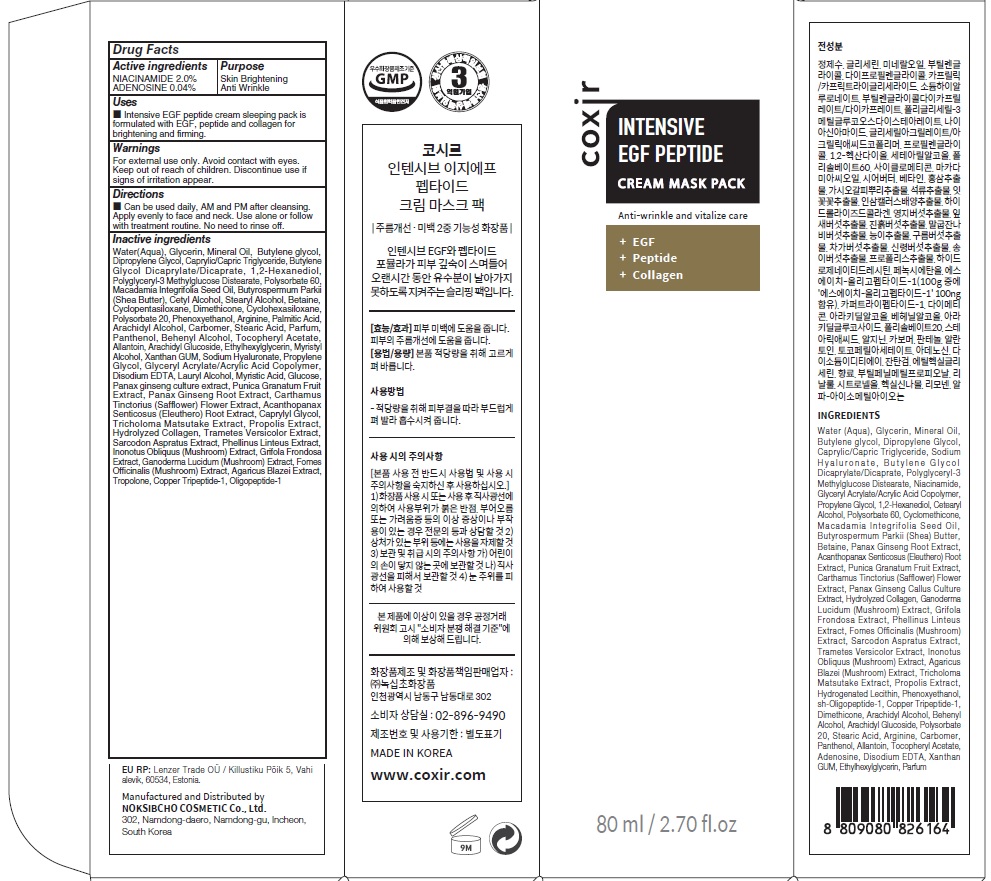 DRUG LABEL: COXIR INTENSIVE EGF PEPTIDE MASK PACK
NDC: 73590-0070 | Form: CREAM
Manufacturer: NOKSIBCHO cosmetic Co., Ltd.
Category: otc | Type: HUMAN OTC DRUG LABEL
Date: 20210714

ACTIVE INGREDIENTS: NIACINAMIDE 1.6 g/80 mL; ADENOSINE 0.03 g/80 mL
INACTIVE INGREDIENTS: Water; Glycerin; Mineral Oil

Drug Facts

ACTIVE INGREDIENTS

NIACINAMIDE 2.0%
ADENOSINE 0.04%

INACTIVE INGREDIENTS

Water(Aqua), Glycerin, Mineral Oil, Butylene glycol, Dipropylene Glycol, Caprylic/Capric Triglyceride, Butylene Glycol Dicaprylate/Dicaprate, 1,2-Hexanediol, Polyglyceryl-3 Methylglucose Distearate, Polysorbate 60, Macadamia Integrifolia Seed Oil, Butyrospermum Parkii (Shea Butter), Cetyl Alcohol, Stearyl Alcohol, Betaine, Cyclopentasiloxane, Dimethicone, Cyclohexasiloxane, Polysorbate 20, Phenoxyethanol, Arginine, Palmitic Acid, Arachidyl Alcohol, Carbomer, Stearic Acid, Parfum, Panthenol, Behenyl Alcohol, Tocopheryl Acetate, Allantoin, Arachidyl Glucoside, Ethylhexylglycerin, Myristyl Alcohol, Xanthan GUM, Sodium Hyaluronate, Propylene Glycol, Glyceryl Acrylate/Acrylic Acid Copolymer, Disodium EDTA, Lauryl Alcohol, Myristic Acid, Glucose, Panax ginseng culture extract, Punica Granatum Fruit Extract, Panax Ginseng Root Extract, Carthamus Tinctorius (Safflower) Flower Extract, Acanthopanax Senticosus (Eleuthero) Root Extract, Caprylyl Glycol, Tricholoma Matsutake Extract, Propolis Extract, Hydrolyzed Collagen, Trametes Versicolor Extract, Sarcodon Aspratus Extract, Phellinus Linteus Extract, Inonotus Obliquus (Mushroom) Extract, Grifola Frondosa Extract, Ganoderma Lucidum (Mushroom) Extract, Fomes Officinalis (Mushroom) Extract, Agaricus Blazei Extract, Tropolone, Copper Tripeptide-1, Oligopeptide-1

PURPOSE

Skin Brightening
Anti wrinkle

WARNINGS

For external use only.
Avoid contact with eyes. Keep out of reach of children.
Discontinue use if signs of irritation appear.

KEEP OUT OF REACH OF CHILDREN

Uses

■ Intensive EGF peptide cream sleeping pack is formulated with EGF, peptide and collagen for brightening and firming.

Directions

■ Can be used daily, AM and PM after cleansing. Apply evenly to face and neck. Use alone or follow with treatment routine.
No need to rinse off.